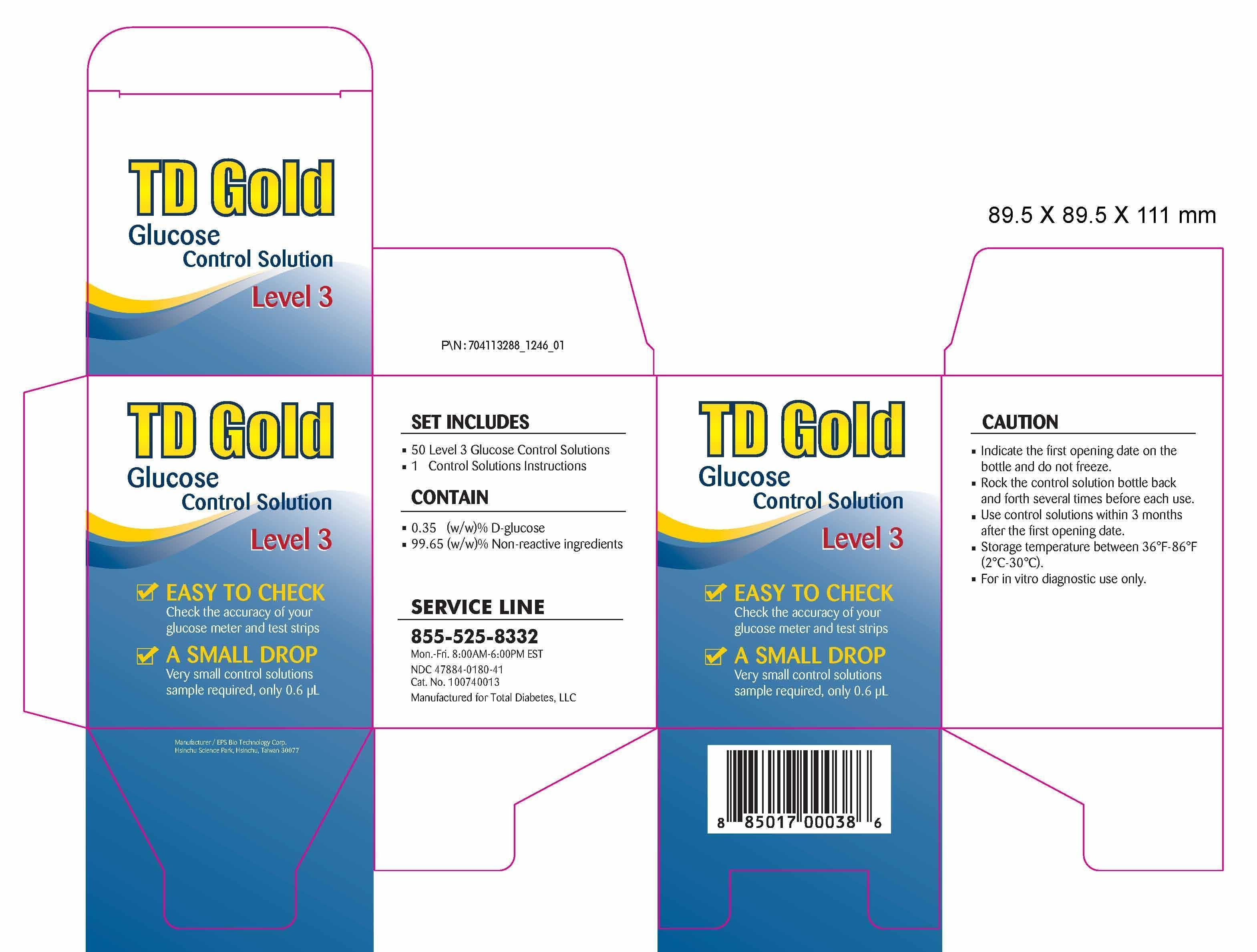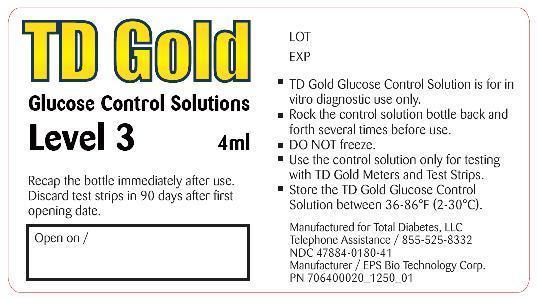 DRUG LABEL: TD Gold Glucose Control Solution Level 3
NDC: 47884-180
Manufacturer: EPS Bio Technology Corp.
Category: other | Type: MEDICAL DEVICE
Date: 20130911

Home Use Medical Device:TD Gold Glucose Control Solution Level 3